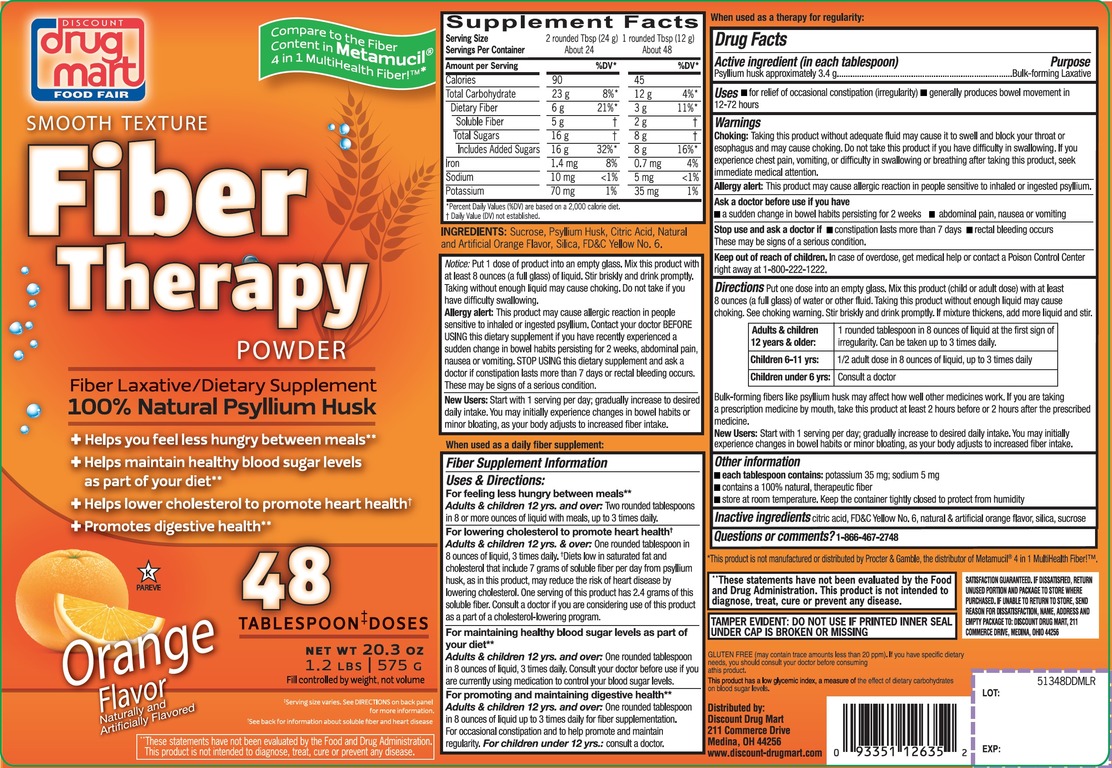 DRUG LABEL: Discount Drug Mart
NDC: 53943-513 | Form: POWDER
Manufacturer: DISCOUNT DRUG MART
Category: otc | Type: HUMAN OTC DRUG LABEL
Date: 20210821

ACTIVE INGREDIENTS: PSYLLIUM HUSK 3.4 g/12 g
INACTIVE INGREDIENTS: ANHYDROUS CITRIC ACID; FD&C Yellow No. 6; SILICON DIOXIDE; SUCROSE

Smooth Texture Natural Fiber Powder Orange Flavor 48 Tablespoon Doses

Drug Facts

Active ingredient: (in each tablespoon)

Psyllium husk approximately 3.4 g

Purpose

Bulk-forming Laxative

Uses:

- for relief of occasional constipation (irregularly)
- Generally produces bowel movement in 12-72 hours.

Warnings:

Choking:

Taking this product without adequate fluid may cause it to swell and block your throat or esophagus and may cause choking. Do not take this product if you have difficulty in swallowing. If you experience chest pain, vomiting, or difficulty in swallowing or breathing after taking this product, seek immediate medical attention.

Allergy alert:

This product may cause allergic reaction in people sensitive to inhaled or ingested psyllium.

Ask a doctor before use if you have

- a sudden change in bowel habits persisting for 2 weeks
- abdominal pain, nausea or vomiting

Stop use and ask a doctor if

- constipation lasts more than 7 days
- rectal bleeding occurs

These may be signs of a serious condition.

Keep out of reach of children. In case of overdose, get medical help or contact a Poison Control Center right away at 1-800-222-1222.

Directions:

Put one dose into an empty glass. Mix this product (child or adult dose) with at least 8 ounces (a full glass) of water or other fluid. Taking this product without enough liquid may cause choking. See choking warning. Stir briskly and drink promptly. If mixture thickens, add more liquid and stir.

Adults & children 12 years & older: | 1 rounded tablespoon in 8 oz of liquid at the first sign of irregularity. Can be taken up to 3 times daily.
Children 6-11 yrs : | ½ adult dose in 8 oz of liquid, up to 3 times daily
Children under 6 yrs: | Consult a doctor

Laxatives, including bilk fibers, may affect how well other medicines work. If you are taking a prescription medicine by mouth, take this product at least 2 hours before or 2 hours after the prescribed medicine. As your body adjusts to increased fiber intake, you may experience changes in bowel habits or minor bloating

New Users:

Start with 1 serving per day; gradually increase to desired daily intake. You may initially experience changes in bowel habits or minor bloating, as your body adjust to increased fiber intake.

Other information:

- each teaspoon contains: potassium 30 mg; sodium 5 mg
- contains 100% natural, therapeutic fiber
- store at room temperature. Keep the container tightly closed to protect from humidity

Inactive ingredients:

citric acid, FD&C Yellow 6, natural and artificial orange flavor, silica, sucrose.

Questions or comments

1-866-467-2748

PRINCIPAL DISPLAY PANEL

NDC 53943-513-72

Compare to the Fiber content in Metamucil® 4 in 1 MultiHealth Fiber™*

SMOOTH TEXTURE

Fiber Therapy

POWDER

Fiber Laxative/Fiber Supplement

100% Natural Psyllium Husk

SUGAR FREE

+ Helps you feel less hungry between meals**
+ Helps maintain healthy blood sugar levels as part of your diet**
+ Helps lower cholesterol to promote heart health†
+ Promotesdigestive health**

Orange Flavor

48 TABLESPOON DOSES

NET WT 20.3 oz 1.2 LBS (575 g)

Fill controlled by weight, not volume

DO NOT USE IF PRINTED INNER SEAL IS BROKEN OR MISSING

*This product is not manufactured or distributed by Procter & Gamble, the distributor of METAMUCIL®.

SATISFACTION GUARANTEED IF DISSATISFIED, RETURN UNUSED PORTION AND PACKAGE TO STORE WHERE PURCHASED. IF UNABLE TO RETURN TO STORE, SEND REASON FOR DISSATISFACTION, NAME, ADDRESS AND EMPTY PACKAGE TO: DISCOUNT DRUG MART, 211 COMMERCE DR., MEDINA, OHIO 44256.

Distributed By:

Drug Mart-Food Fair

211 Commerce Dr.

Medina, Ohio 44256